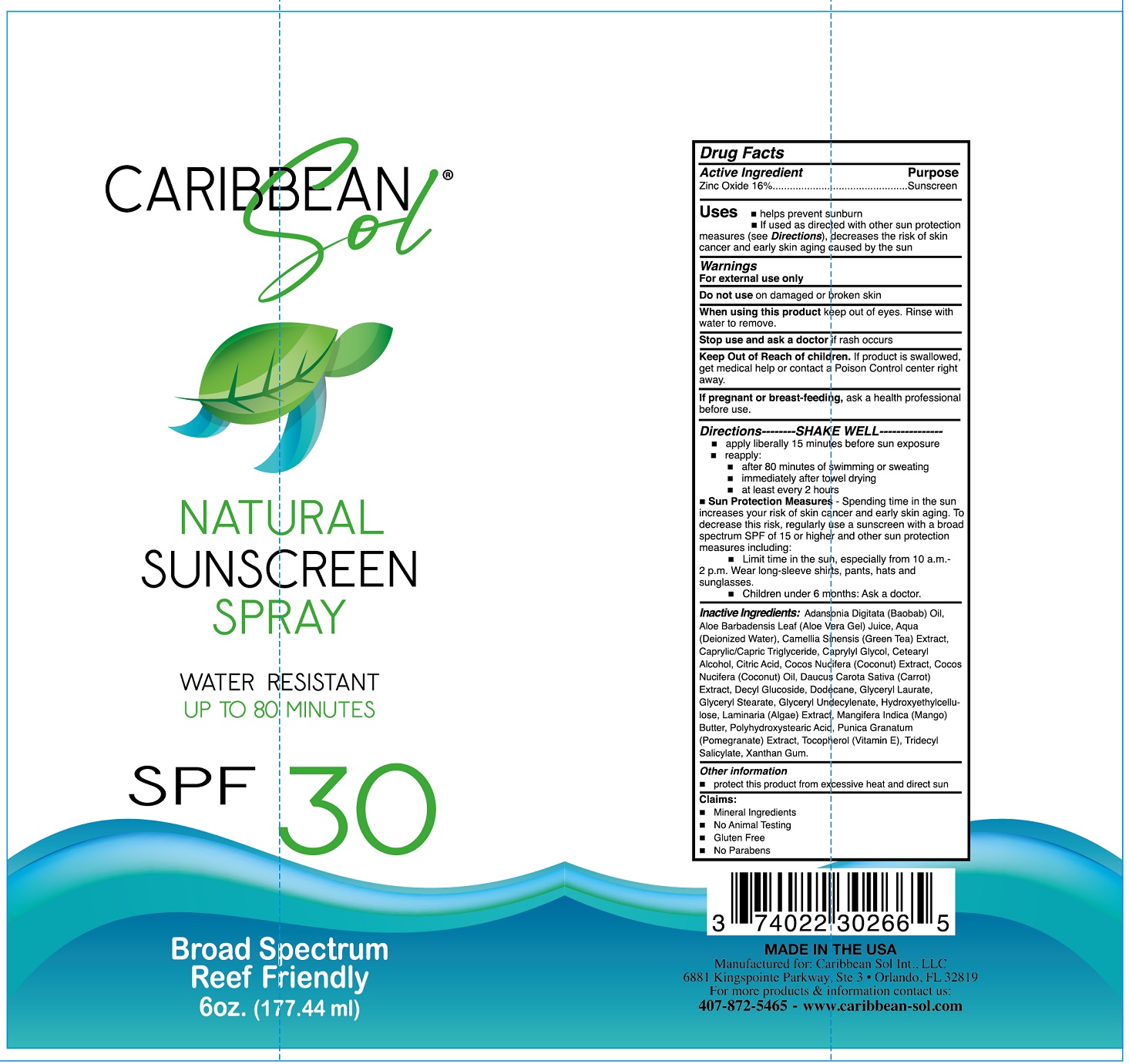 DRUG LABEL: CARIBBEAN SOL Natural Sunscreen SPF-30
NDC: 82520-264 | Form: SOLUTION
Manufacturer: Caribbean Sol International, LLC
Category: otc | Type: HUMAN OTC DRUG LABEL
Date: 20231111

ACTIVE INGREDIENTS: ZINC OXIDE 160 mg/1 mL
INACTIVE INGREDIENTS: ADANSONIA DIGITATA SEED OIL; ALOE VERA LEAF; WATER; GREEN TEA LEAF; MEDIUM-CHAIN TRIGLYCERIDES; CAPRYLYL GLYCOL; CETOSTEARYL ALCOHOL; CITRIC ACID MONOHYDRATE; COCONUT; COCONUT OIL; CARROT; DECYL GLUCOSIDE; DODECANE; GLYCERYL LAURATE; GLYCERYL MONOSTEARATE; HYDROXYETHYL CELLULOSE, UNSPECIFIED; MANGO; PUNICA GRANATUM ROOT BARK; TOCOPHEROL; TRIDECYL SALICYLATE; XANTHAN GUM

CARIBBEAN SOL Natural Sunscreen Spray SPF-30

Active Ingredient

Zinc Oxide 16%

Purpose

Sunscreen

Uses

- helps prevent sunburn
- if used as directed with other sun protection measures (see), decreases the risk of skin cancer and early skin aging caused by the sun Directions

Warnings

For external use only

Do not use

on damaged or broken skin

When using this product

keep out of eyes. Rinse with water to remove.

Stop use and ask a doctor

if rash ocuurs

Keep out of Reach of children.

If product is swallowed, get medical help or contact a Poison Control center right away.

If pregnant or breast-feeding,

ask a health professional before use.

Directions-------SHAKE WELL--------

- apply liberally 15 minutes before sun exposure
- reapply:
- after 80 minutes of swimming or sweating
- immediately after towel drying
- at least every 2 hours
- Spending time in the sun increases your risk of skin cancer and early skin aging. To decrease this risk, regularly use a sunscreen with a broad spectrum SPE of 15 or higher and other sun protection measures including: Sun Protection Measures -
- Limit time in the sun, especially from 10 a.m.-2 p.m. Wear long-sleeve shirts, pants, hats and sunglasses.
- Children under 6 months: Ask a doctor.

Inactive Ingredients:

Adansonia Digitata (Baobab) Oil, Aloe Barbadensis Leaf (Aloe Vera Gel) Juice, Aqua (Deionized Water), Camellia Sinensis (Green Tea) Extract, Caprylic/Capric Triglyceride, Caprylyl Glycol, cetearyl Alcohol, Citric Acid, Cocos Nucifera (Coconut) Extract, Cocos Nucifera (Coconut) Oil, Daucus Carota Sativa (Carrot) Extract, Decyl Glucoside, Dodecane, Glyceryl Laurate, Glyceryl Stearate, Glyceryl Undecylenate, Hydroxyethylcellu-lose, Laminaria (Algae) Extract, Mangifera Indica (Mango) Butter, Polyhydroxystearic Acid, Punica Granatum (Pomegranate) Extract, Tocopherol (Vitamin E), Tridecyl Salicylate, Xanthan Gum.

Other information

protect this product from excessive heat and direct sun

Claims:

- Mineral Ingredients
- No Animal Testing
- Gluten Free
- No Parabens